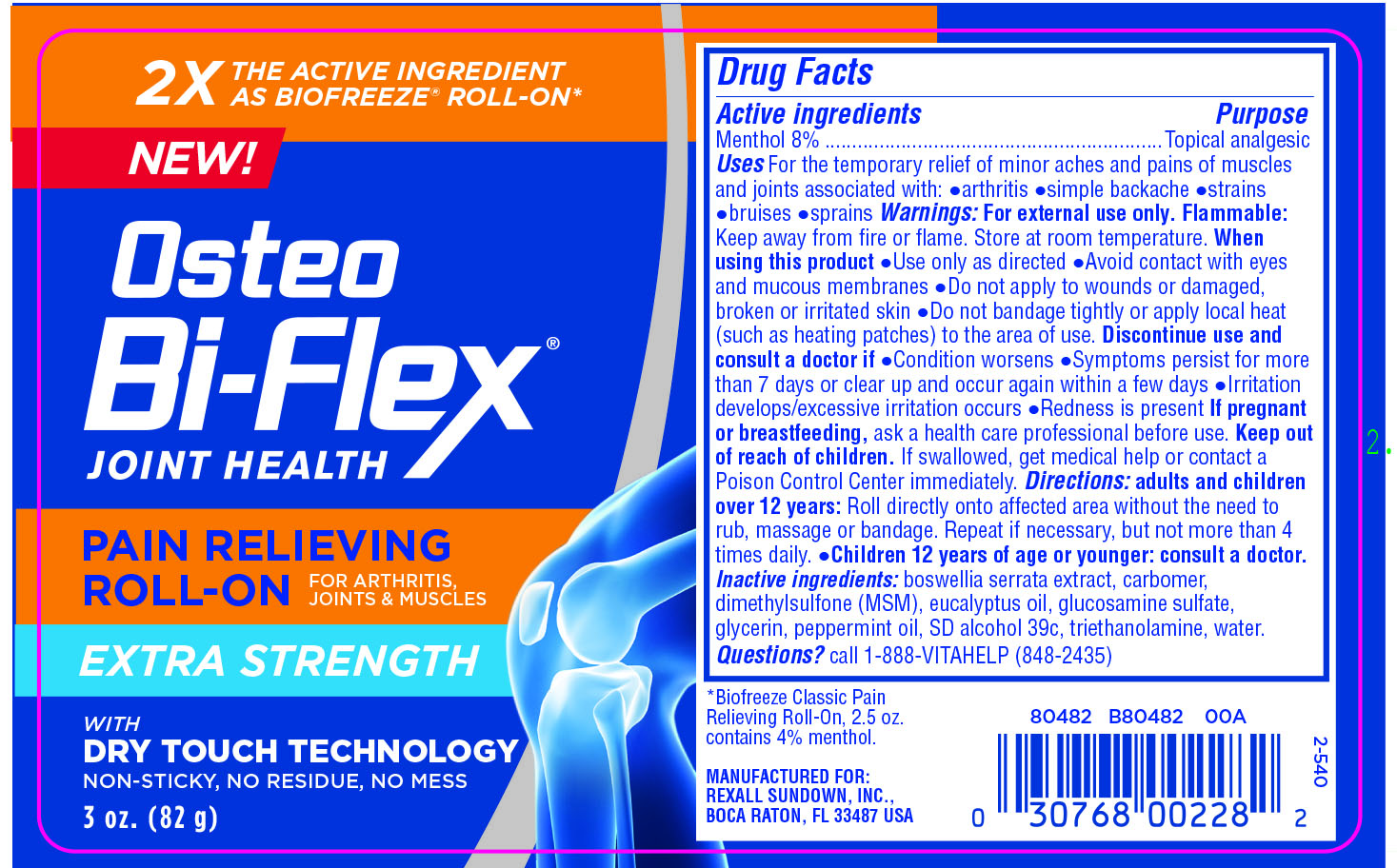 DRUG LABEL: Osteo Bi-Flex Roll-on
NDC: 24737-1901 | Form: CREAM
Manufacturer: The Nature's Bounty Company
Category: otc | Type: HUMAN OTC DRUG LABEL
Date: 20181219

ACTIVE INGREDIENTS: MENTHOL 8 g/100 g
INACTIVE INGREDIENTS: ALCOHOL 54 g/100 g; WATER 29.5 g/100 g

Active ingredients

Menthol 8% ..............................................................Topical analgesic

Purpose

Purpose: Topical analgesic

Uses

For the temporary relief of minor aches and pains of muscles
and joints associated with: ●arthritis ●simple backache ●strains
●bruises ●sprains

Warnings: For external use only.

Flammable: Keep away from fire or flame. Store at room temperature.

When using this product

●Use only as directed

●Avoid contact with eyes and mucous membranes

●Do not apply to wounds or damaged, broken or irritated skin

●Do not bandage tightly or apply local heat (such as heating patches) to the area of use.

Discontinue use and consult a doctor if

●Condition worsens

●Symptoms persist for more than 7 days or clear up and occur again within a few days

●Irritation develops/excessive irritation occurs

●Redness is present

If pregnant or breastfeeding, ask a health care professional before use.

Keep out of reach of children

If swallowed, get medical help or contact a Poison Control Center immediately.

Directions:

Directions: adults and children over 12 years: Roll directly onto affected area without the need to rub, massage or bandage. Repeat if necessary, but not more than 4 times daily.

Directions

Directions: adults and children over 12 years: Roll directly onto affected area without the need to rub, massage or bandage. Repeat if necessary, but not more than 4 times daily. ●Children 12 years of age or younger: consult a doctor.

Inactive ingredients:

Inactive ingredients: boswellia serrata extract, carbomer, dimethylsulfone (MSM), eucalyptus oil, glucosamine sulfate, glycerin, peppermint oil, SD alcohol 39c, triethanolamine, water.

Questions?

Call 1-888-VITAHELP (848-2435)

PACKAGE LABEL

Osteo BiFlex

Joint Health

PAIN RELIEVING
ROLL-ON FOR ARTHRITIS, JOINTS & MUSCLES
With DRY TOUCH TECHNOLOGY NON-STICKY, NO RESIDUE, NO MESS